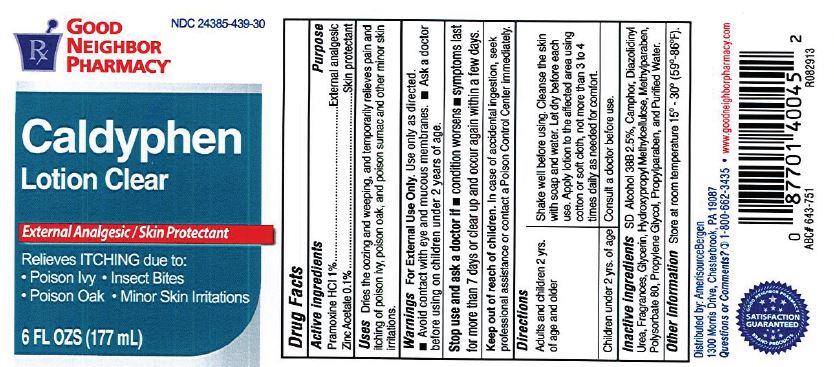 DRUG LABEL: Caldyphen Clear
NDC: 24385-439 | Form: LOTION
Manufacturer: Amerisource Bergen
Category: otc | Type: HUMAN OTC DRUG LABEL
Date: 20200621

ACTIVE INGREDIENTS: PRAMOXINE HYDROCHLORIDE 10 mg/1 mL; ZINC ACETATE 1 mg/1 mL
INACTIVE INGREDIENTS: CAMPHOR (NATURAL); DIAZOLIDINYL UREA; GLYCERIN; HYPROMELLOSE, UNSPECIFIED; METHYLPARABEN; POLYSORBATE 80; PROPYLENE GLYCOL; PROPYLPARABEN; WATER

Caldyphen Clear

Drug Facts

Active Ingredient

Pramoxine HCl 1%

Purpose

External analgesic

Active Ingredient

Zinc Acetate 0.1%

Purpose

Skin protectant

Uses

Dries the oozing and weeping, and temporarily relieves pain and itching of poison ivy, poison oak, and poison sumac and other minor skin irritations.

Warnings

For External Use Only. Use only as directed. Avoid contact with eye and mucous membranes. ask a doctor before using on children under 2 years of age.

Stop use and as a doctor if

condition worsens. Symptoms last for more than 7 days or celar up and occur again whitin a few days.

Keep out of reach of children

In case of accidental ingestion, seek professional assistance or contact a Poison Control Center immediately.

Directions

Adults and children 2 yrs. of age and older. Shake well before using. cleanse the skin with soap and water. Let dry before each use. apply lotion to the affected area using cotton or soft cloth, not more than 3 to 4 times daily as needed for comfort.

children unedr 2 yrs. of age. Consult a doctor before use.

Inactive Ingredients

SD alcohol 38B 2.5%, Camphor, Diazolidinyl Urea, Fragrances, Glycerin, Hydroxypropyl Methylcellulose, Methylparaben, Polysorbate 80, Propylene Glycol, Propylparaben, and Purified Water.

Other information

Store at room temperature 15 - 30 (59-86F)

Distributed by: AmerisourceBergen

1300 Morris Drive, Chesterbrook, PA 19087

Questions or comments?

1-800-662-3435 www.goodneighborpharmacy.com